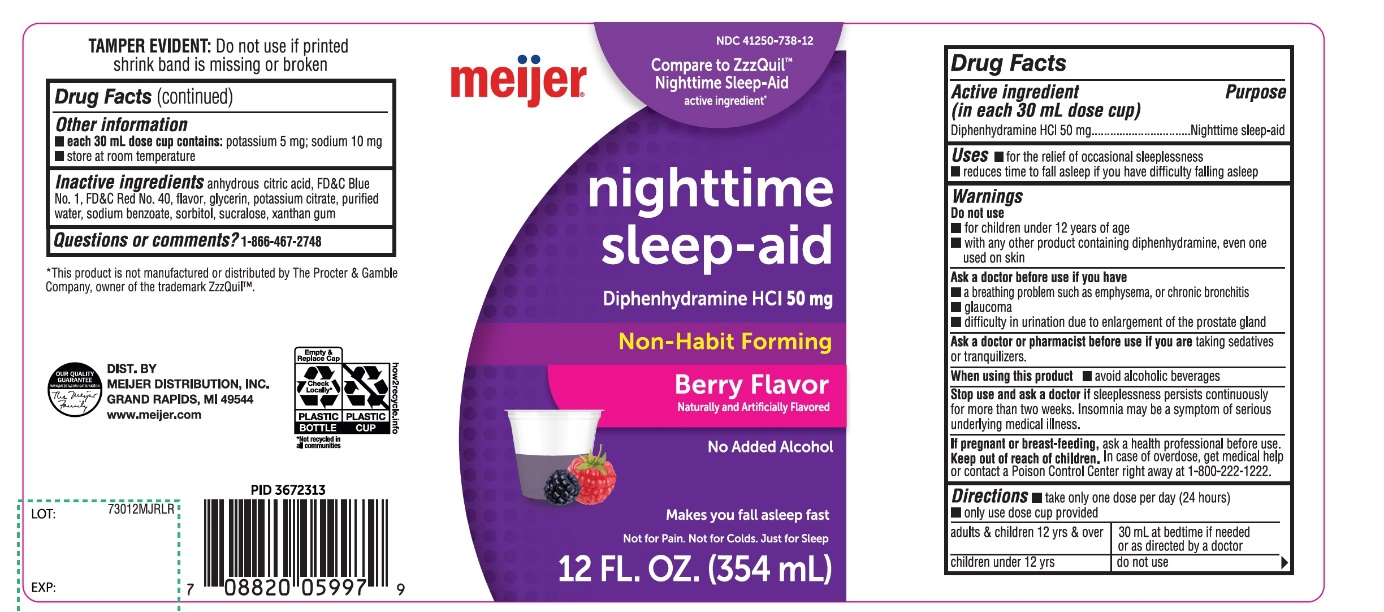 DRUG LABEL: Meijer Nighttime Sleep-aid

NDC: 41250-738 | Form: SOLUTION
Manufacturer: MEIJER DISTRIBUTION INC
Category: otc | Type: HUMAN OTC DRUG LABEL
Date: 20251024

ACTIVE INGREDIENTS: DIPHENHYDRAMINE HYDROCHLORIDE 50 mg/30 mL
INACTIVE INGREDIENTS: ANHYDROUS CITRIC ACID; FD&C BLUE NO. 1; FD&C RED NO. 40; GLYCERIN; POTASSIUM CITRATE; WATER; SODIUM BENZOATE; SORBITOL; SUCRALOSE; XANTHAN GUM

meijer Alcohol-Free Nighttime Sleep-Aid Diphenhydramine HCl

Drug Facts

Active ingredient (In each 30 mL)
Diphenhydramine HCl 50 mg

Purpose

Nighttime sleep-aid

Uses

- for the relief of occasional sleeplessness
- reduces time to fall asleep if you have difficulty falling asleep

Warnings

Do not use

- for children under 12 years of age
- with any other product containing diphenhydramine, even one used on skin

Ask a doctor before use if you have

- a breathing problem such as emphysema, or chronic bronchitis
- glaucoma
- difficulty in urination due to enlargement of the prostate gland

Ask a doctor or pharmacist before use if you aretaking sedatives or tranquilizers.
When using this product

- avoid alcoholic beverages

Stop use and ask a doctor ifsleeplessness persists continuously for more than two weeks. Insomnia may be a symptom of serious underlying medical illness.
If pregnant or breast-feeding,ask a health professional before use.

Keep out of reach of children.

Overdose warning:In case of overdose, get medical help or contact a Poison Control Center right away (1-800-222-1222).

Directions

- take only one dose per day (24 hours)
- measure with dosing cup provide

adults & children 12 yrs & over | One Dose = 30 mL at bed time if needed or as directed by a doctor
Children under 12 yrs | do not use

Other information

- each 30 mL dose contains: sodium 23 mg
- store at room temperature
- protect from light. Does not meet USP requirement for light-resistant packaging.

Inactive ingredients

anhydrous citric acid, FD&C Blue #1, FD&C Red #40, glycerin, natural and artificial flavor, potassium citrate, purified water, sodium benzoate, sorbitol, sucralose, xanthan gum.

Questions or comments?

1-866-467-2748

PACKAGE LABEL-PRINCIPAL DISPLAY PANEL 12 FL OZ (354 mL Bottle)

meijer®
NDC# 41250-738-12
Compare to Zzzquil®Nighttime Sleep-Aid* active ingredient*

Nighttime Sleep-aid
Diphenhydramine HCl 50 mg

- Non-Habit Forming

Alcohol-Free

Not for treating Cold or Flu, See Warnings
Berry Flavor

Naturally and Artificially Flavored
12 FL OZ (354 mL)

MEIJER PHARMACIST RECOMMENED

MONEY BACK GURANTEE

DIST. BY MEIJER DISTRIBUTION, INC.

GRAND RAPIDS, MI 49544

www.meijer.com*This product is not manufactured or distributed by The Procter & Gamble Company, owner of the registered trademark ZzzQuil®.